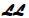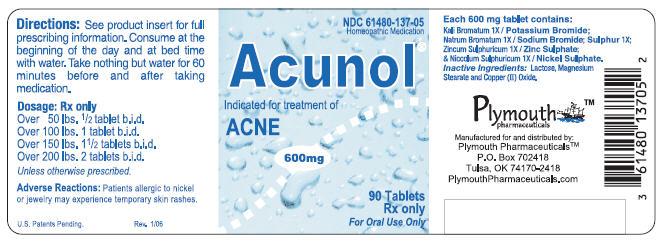 DRUG LABEL: Acunol
NDC: 61480-137 | Form: TABLET
Manufacturer: PLYMOUTH HEALTHCARE PRODUCTS LLC
Category: homeopathic | Type: HUMAN PRESCRIPTION DRUG LABEL
Date: 20250107

ACTIVE INGREDIENTS: NICKEL SULFATE 1 [hp_X]/1 1; POTASSIUM BROMIDE 1 [hp_X]/1 1; SODIUM BROMIDE 1 [hp_X]/1 1; ZINC SULFATE ANHYDROUS 1 [hp_X]/1 1; SULFUR 1 [hp_X]/1 1

Acunol™

CAUTION

Federal law prohibits dispensing without a prescription.

DESCRIPTION

Acunol™ is a biochemical homeopathic medication indicated for the treatment of acne.^32-34The active ingredients in each Acunol™ tablet consist of the following: Potassium Bromide (Kali Bromatum) 1X, Sodium Bromide (Natrum Bromatum) 1X, Zinc Sulphate (Zincum Sulphuricum) 1X, Sulphur 1X, and Nickel Sulphate (Niccolum Sulphuricum) 1X. These drug ingredients are listed in the Homoeopathic Pharmacopoeia of the United States (HPUS).^1

Inactive ingredients: Lactose, Magnesium Stearate, and Copper (II) Oxide.

Pharmacological class:Homeopathic drug.

Dosage form:Oral 600 mg scored tablet. May be swallowed whole, chewed or dissolved in the mouth and swallowed.

CLINICAL PHARMACOLOGY

The active ingredients in Acunol™ are simple biochemical compounds. The exact mechanism of action is unknown; however, it is known that bromide enhances phagocytic and bactericidal activity of neutrophils.^31

POTASSIUM BROMIDE & SODIUM BROMIDEdissolve and dissociate in the digestive tract into their ionic constituents. Each tablet contains approximately 30 mg of bromide (calculated). Ionic bromide is rapidly and completely absorbed from the intestine and distributed almost exclusively in the extracellular fluids.^7,8Bromide is eliminated by the kidneys and the elimination half-life is 11-12 days.

ZINC SULPHATEdissolves and dissociates in the digestive tract into its ionic constituents. Each tablet contains approximately 5 mg of zinc (calculated). Zinc is an essential trace mineral necessary for protein synthesis, enzyme stimulation, and alkaline balance.^27,28It is primarily absorbed from the duodenum and excreted via feces, urine, and sweat.^26

SULPHURis a naturally occurring mineral that is an essential part of the human body. It exhibits anti-bacterial, anti-parasitic, fungicidal, and keratolytic properties.^26Each tablet contains approximately 5 mg of sulphur (calculated). Sulphur is highly water soluble and as a result is easily excreted by the body via sweat and urine.^22Since the sulphur found in Acunol™ is a naturally occurring mineral, it is radically different from sulfa drugs (sulfonamide antibiotics). Therefore, patients who are allergic to sulfa drugs CAN safely take Acunol™.

NICKEL SULPHATEdissolves and dissociates in the digestive tract into its ionic constituents. Each tablet contains approximately 0.5 mg of ionic nickel (calculated). According to studies, 15% to 50% of ionic nickel is absorbed on a fasted stomach.^2Food markedly decreases the rate and extent of nickel absorption.^3,4Clinical studies show that serum concentrations of nickel are variable among patients after administering the same dosage.^5Peak serum nickel concentration is reached about two hours after oral administration. Nickel is in its highly stable divalent cation state and is therefore not expected to be metabolized to any significant degree in the body. Absorbed nickel is primarily excreted in the urine and elimination half-life is about 21 hours.^3,5Renal clearance is rapid and efficient, and nickel does not accumulate in the body.^6

CLINICAL STUDIES

A variety of controlled clinical studies have been performed using various sources of both nickel and bromide in over 300 subjects. Clinical efficacy and safety have been documented in a significant number of subjects. Published and unpublished reports are available upon request.^9,20,21

INDICATIONS

Acunol™ is indicated for the treatment of mild to moderate acne vulgaris, acne rosacea, peri-oral dermatitis, and folliculitis. It has been found to work well with a variety of combination therapies.

CONTRAINDICATIONS

Although there are no known contraindications, patients who are allergic to any Acunol™ ingredient should consult a physician prior to taking the medication. (Refer to Section on Hypersensitivity)

WARNING

Do not use if imprinted seal under bottle cap is missing or broken. Do not use if pregnant or nursing. If allergic to nickel or metal objects such as jewelry, see PRECAUTIONSfor hypersensitivity information. Lactose intolerant patients may have gastrointestinal difficulty. This has very rarely been reported at the doses used.

PRECAUTIONS

Carefully adjust dosage to weight when treating young children. Use cautiously in setting of kidney disease. (see Dosage and Administration) If skin rash appears or if nervous symptoms persist, recur frequently, or are unusual, discontinue use.

Hypersensitivity

Caution should be used when administering to patients with a history of contact sensitivity to nickel (common metal exposure) or if there is a history of vesicular hand eczema (dyshidrosis, pomphylox). Nickel allergy may be confirmed by a positive nickel patch test. Most patients with hand eczema, positive nickel allergy history, or a positive nickel patch test do nothave any untoward reaction to administration of Acunol™. If there is a history of nickel sensitivity or dyshidrotic hand eczema, begin with a very low dose and slowly increase to a recommended starting dose over a period of 5 weeks as tolerated, thus allowing progressive GI absorption*.

*Nickel desensitization schedule:
Week | Amount of Time to Take Medication Prior to Breakfast
Week 1 | With Breakfast
Week 2 | 15 min Prior
Week 3 | 30 min Prior
Week 4 | 45 min Prior
Week 5 and thereon | 1 hour Prior

If new pruritic rashes occur or persist, discontinue Acunol™ and treat appropriately. Do not use if there is a history of extra-cutaneous hypersensitivity to nickel or any ingredient in Acunol™.

Information for patients

Patients using Acunol™ should receive the following information and instructions:

1. This medication is to be used as directed by a physician.
2. It is important to take orally at the beginning of the day on an empty stomach and at the end of the day before bed; take nothing but water for one hour afterwards to avoid interference with absorption.

Drug interactions

There are no known drug interactions. Since copper deficiency in human nutrition has occasionally been induced by supplemental zinc therapy, copper has been added in order to minimize this rare occurrence. (see Inactive ingredients) For Tetracycline or Quinolones co-administration with Acunol, see Dosage and Administration

Carcinogenesis, mutagenesis, impairment of fertility

No studies have been done on the carcinogenesis, mutagenesis, or impairment of fertility of Acunol™. No carcinogenesis or mutagenesis has been reported in multiple animal studies for oral administration of soluble nickel and bromide salts (active ingredients) even at very high doses.^10-14

Effects of soluble potassium bromide

KBr is not listed as a carcinogen by the NTP, IARC, and OSHA.^16

Effects of sodium bromide

NaBr is not listed as a carcinogen by the IARC, NTP, or OSHA.^35

Effects of zinc sulphate

ZnSO4is not listed as a carcinogen by the ACGIH, IARC, NTP, or CA Prop 65.^29

Effects of sulphur

Sulphur is not listed as a carcinogen by the ACGIH, IARC, NIOSH, NTP, or OSHA.^25

Effects of soluble nickel sulphate

Studies on experimental animals have never indicated that nickel, at any dose, is a carcinogen when introduced to the body orally. Furthermore, Nickel sulphate has never been known to induce carcinogenesis via any route of introduction including: oral, inhalation, cutaneous, IM, or IP.^10-12,15No adverse effects were noted on fertility or reproduction in a 3-generational study of albino Wistar rats fed up to 1000 ppm Ni per day, which is equivalent to 50 mg/kg per day Ni.^15

Pregnancy

Pregnancy category C

Animal reproduction studies have not been conducted with Acunol™. Acunol™ should not be given to a pregnant woman.

Nursing mothers

It is not known whether this drug is excreted in human milk. However, since many drugs are excreted in human milk, caution should be exercised when Acunol™ is administered to a nursing woman.

Pediatric use

Carefully adjust dosage to weight when treating young children.

ADVERSE REACTIONS

Acunol™ contains low doses of active ingredients. Therefore there are minimal known side effects. (see PRECAUTIONSfor hypersensitivity information)

OVERDOSAGE

Bromide toxicity

Indications of toxicity due to oral overdosage of bromide may include nausea, vomiting, apathy, disturbed coordination, loss of memory, drowsiness, loss of emotional control, agitation, hallucination, tremors, depressed reflexes, stupor, and coma. Acute toxic reactions in humans have been reported at doses as low as 1000 mg.^19This level is 33 times the dose received in one tablet of Acunol™.

Zinc sulphate toxicity

Symptoms of acute toxicity of zinc due to oral overdoseage can include dehydration, stomach pain, lethargy, dizziness, muscular incoordination, and in severe cases renal failure.^26Chronic zinc toxicity can occur at levels of 100-300 mg/d.^30

Sulphur toxicity

The oral rat LD50for sulphur is reported to be greater than 5,000 mg/kg.^23This is more than 11,000 times the maximum dose recommended for Acunol™. Ingestion of toxic levels of sulphur can cause sore throat, nausea, headache, gastrointestinal irritation, and possibly unconsciousness in severe cases.^24,25Sulphur poses such a remote risk that is placed in the lowest toxic category possible, EPA Toxicity Category IV.^23

Nickel sulphate toxicity

The oral rat LD50for nickel sulphate hexahydrate is 275 mg/kg.^17Symptoms of toxicity due to oral overdosage of nickel sulphate may include nausea, vomiting, abdominal discomfort, diarrhea, giddiness, lassitude, headaches, cough, and shortness of breath.^18The lowest observed transitory toxic effects from human ingestion of soluble nickel salts is approximately 8 mg nickel/kg body weight.^18This is 180 times the maximum dose recommended for Acunol™. (See below)

DOSAGE AND ADMINISTRATION

Take tablets twice a day (b.i.d.) for best results. Absorption of nickel sulphate is variable among individuals. For maximum nickel absorption, tablets should be taken orally upon rising at the beginning of the day and at the end of the day before bed.Take nothing but water for one hour after taking medication to aid nickel absorption. If taking Tetracycline or Levofloxacin allow at least two hours after taking Acunol. If taking a different Quinolone antibiotic, consult manufacturer's information.

Kg | lbs | Starting dose | Max Daily dose
23-45 | 51-100 | ½ ∙ b.i.d. | 1 ∙ b.i.d.
46-68 | 101-150 | 1 ∙ b.i.d. | 2 ∙ b.i.d.
69-90 | 151-200 | 1½ ∙ b.i.d. | 3 ∙ b.i.d.
91+ | 201+ | 2 ∙ b.i.d. | 4 ∙ b.i.d.

Increase dose only if needed on a monthly basis up to the max daily dose. Treatment dose and duration depends on the individual.

In the setting of significant renal impairment

Dosage should be adjusted and serum nickel and bromide levels should be followed. Steady state trough nickel level should be drawn priorto ingesting the day's dose after one week of dosing or at appropriate intervals. Target trough serum nickel level is 10-40 mcg/L. (Caution: post dose peak levels are unreliable.) Serum bromide assay by spectrophotometry is the historic standard.^36Concentrations higher than 50 mg/dl may be compatible with toxicity. No therapeutic target levels exist for bromide.

HOW SUPPLIED

Scored tablets, off white in color with green speckles, with imprinted on one side and a score on the other side, in child-resistant and tamper-resistant bottles of 90. NDC 61480-137-05

REFERENCES

1. The Homeopathic Pharmacopoeia of the United States (HPUS), 8thEdition, Falls Church, Virginia, 1979.
2. Sunderman FW jr., Biological monitoring of nickel in humans. Scand J Work Environ Health 1993; 19 suppl 1:34-38.
3. Sunderman FW jr., Hopfer SM, Sweeny KR, Marcus AH, Most BM, Creason J. Nickel absorption and kinetics in human volunteers, P.S.E.B.M. 1989; 191:5-11.
4. Solomons NW, Viteri F, Shuler TR, Nielsen FH. Bioavailability of nickel in man: Effects of foods and chemically-defined dietary constituents on the absorption of inorganic nickel. J Nutr 1982; (2); 112; 39-50.
5. Christensen OB, lagesson V. Nickel concentration of blood and urine after oral administration. Annals of Clinical and Laboratory Science 1981;2(2);119-125.
6. Nielsen FH. Is nickel nutritionally important? Nutrition Today 1993;28(1):14-19.
7. Vaiseman N, Koren G, Pencharz P. Pharmacokinetics or oral and intravenous bromide in normal volunteers. Clinical Toxicology 1986;24(5):403-413.
8. Van Leeuwen FXR, Sangster B. The toxicology of bromide ion. CRC Critical Reviews in Toxicilogy 1987; 18(3):189-213.
9. Smith SA. Oral supplementation of nickel and bromide in psoriasis vulgaris using nickel sulfate and sodium bromide. 1995 (unpublished report).
10. Miller MJ, Bogdan KG, Leach JF, and Gray AJ. Ambient air criteria document, Bureau of Toxic Substance Assessment, New York Department of Health, Albany, NY 1989.
11. US EPA, Environmental Criteria and Assessment Office, Office of Health and Environmental Assessment, health assessment document for nickel and nickel compounds. Washington DC, EPA/600/8-83/012FF.
12. US EPA, Environmental Criteria and Assessment Office, Office of health and Environmental Assessment. Drinking water quantification of toxicological effects for nickel. ECAO-CIN-443. 1991.
13. US FDA, Center for Food Safety and Applied Nutrition. Guidance document for nickel in shellfish. 1993.
14. Buselmaier W. von, Rohrborn G, and Propping G. Mutagenitats – Untersuchugen mit Pestiziden im Host – Mediated Assay und mit dem Dominanten Letaltest an der Maus. Biol Zbl 1972; 91:311-325.
15. Ambrose AM, Larson PS, Borzelleca JF, and Hennigar GR, Jr. Long term toxicologic assessment of nickel in rats and dogs. Journal of Food Science and Technology 1976;13:181-187.
16. MSDS Sheet No. 247 Potassium Bromide. Schenectady, NY: Genium Publishing Corp 1991.
17. MSDS Sheet No. 37 Nickel Sulfate. Schenectady, NY: Genium Publishing Corp 1993.
18. Sunderman FW Jr., Dingle B, Hopfer SM, and Swift T. Acute nickel toxicity in electroplating workers who accidentally ingested a solution of nickel sulfate and nickel chloride. American Journal of Industrial Medicine 1988;14;257- 266.
19. Martindale: The Extra Pharmacopoeia 27thed. Wade A, editor. The Pharmaceutical Press: London, 1977, pp273-274.
20. Smith SA, et al, Improvement of Psoriasis Vulgaris with Oral Nickel Dibromide. Archives of Dermatology 1997; 133:661-663.
21. Smith SA, Baker AE, etal. Effective Treatment of Seborrheic Dermatitis Using a Low Dose, Oral Homeopathic Medication... Alt Med Rev 2002; 7, pp59-67.
22. MSM- The Wonder Supplement of the Millennium. <http://www.eftel.com.au/~mcs/msm/msm> 7 July 2005.
23. Pesticide Information Profile: Sulfur. <http://pmep.cce.cornell.edu/profiles/extoxnet/pyrethrins-ziram/sulfurext.. html> 7 July 2005.
24. MSDS Number 58138: Sulfur. 12 Feb. 2004 Mallinckrodt Baker, Inc. 7 July 2005 <http://www.jtbaker.cvom/msds/englishhtml/s8138.htm>.
25. MSDS Sulfur: Hazardous According to Criteria of Worksafe Australia. Dec. 1998. Seton Compliance Resource Center <http://www.setonresource.center.com>.
26. Remington: The Science and Practice of Pharmacy. 19thEdition, Mack Publishing Company, 1995.
27. Zinc.T.J.Clark.19July2005.<http://www.mailguard.org/MINERALS/zinc.htm>.
28. The Benefits of Zinc. Dr. George Obikoya. 2004. The Vitamins & Nutrition Center. 19 July 2005 <http://www.vitamins-nutrition.org/vitamins/zinc.html>.
29. Material Safety Data Sheet: Zinc sulfate. 11/18/2004. Fisher Scientific. 19 Dec. 2005 <http://fscimage.fishersci.com/msds/89980.htm>.
30. Zinc. Pharmavite®LLC. 2003-2005. Vitamin & Herb University. 19 July 2005. <http://www.vitaminherbuniversity.com/topic.asp?categoryid=2&topicid=1029>.
31. Steele RW, Woody RC. Enhanced Neutrophil Function in Children on Bromide Therapy. American Journal of Medical Sciences 1991; 302(3): 145 – 147.
32. Reckeweg, Hans-Heinrich, Materia Medica, 1983, first English edition.
33. Boericke, William, Materia Medica with Reperatory, 1927, ninth edition.
34. Clarke, John Henry, A Dictionary of Practical Materia Medica, 1921, reprint edition 1996.
35. MSDS Sheet No. 743 Sodium Bromide. Schenectady, NY: Genium Publishing Corp 1991.
36. Sonnenwirth AC, Jarett L, eds. Bromide. In: Gradwohl's Clinical Laboratory Methods and Diagnosis, 1980; Vol. 1, Ch. 19, Analytical Toxicology, 401-402.

RxSales@PlymouthPharmaceuticals.com

www.PlymouthPharmaceuticals.com

Plymouth Pharmaceuticals Inc. dba LOMA LUX Laboratories; P.O. BOX 702418; Tulsa, OK 74170-2418

Phone 800.316.9636, 918.664.9882, Fax 918.664.9884

Revised 09.13.06 TDS

PRINCIPAL DISPLAY PANEL - 90 Tablet Label

NDC 61480-137-05
Homeopathic Medication

Acunol®

Indicated for treatment of
ACNE

600mg

90 Tablets
Rx only
For Oral Use Only